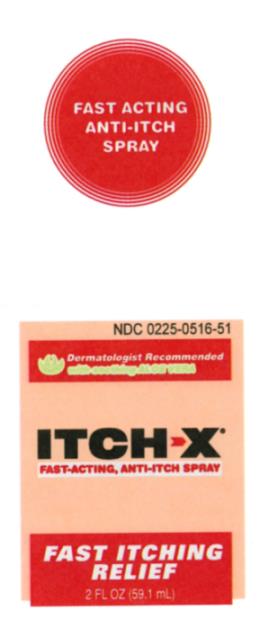 DRUG LABEL: ITCH-X
NDC: 0225-0516 | Form: SPRAY
Manufacturer: BF ASCHER AND CO INC
Category: otc | Type: HUMAN OTC DRUG LABEL
Date: 20221102

ACTIVE INGREDIENTS: PRAMOXINE HYDROCHLORIDE 1 g/100 mL; BENZYL ALCOHOL 10 g/100 mL
INACTIVE INGREDIENTS: WATER; ALOE; ALCOHOL

Itch-X Spray

Active ingredients.............. Purpose
(in solution)
Benzyl alcohol 10%............Topical analgesic
Pramoxine HCl 1%..............Topical analgesic

INDICATIONS AND USAGE

Uses temporarily relieves pain and itching associ- ated with insect bites, minor burns, sunburn, minor cuts, scrapes, minor skin irritations, hives and rashes due to poison ivy, poison oak, or poison sumac.

PURPOSE

Uses temporarily relieves pain and itching associ- ated with insect bites, minor burns, sunburn, minor cuts, scrapes, minor skin irritations, hives and rashes due to poison ivy, poison oak, or poison sumac.

Warnings

For external use only.
Avoid contact with eyes.
Keep away from fire or flame.

ASK DOCTOR

If condition worsens, or if symptoms persist for more than 7 days or clear up and occur again within a few days, discontinue use and consult a physician.

DO NOT USE

Do not apply to open wounds, damaged, or blistered skin.

Do not use for vaginal, genital, or rectal itching.

Do not use on children under 2 years of age unless under the advice and supervision of a physician.

PREGNANCY OR BREAST FEEDING

If pregnant or breast-feeding, ask a health professional before use.

KEEP OUT OF REACH OF CHILDREN

Keep this and all drugs out of reach of children. In case of overdose or ingestion of contents, get medical help or contact a poison control center immediately.

Directions

- Adults and children 2 years and older: apply to affected area not more than 3 or 4 times daily.
- Children under 2 years: consult a physician.

Other information

- store at 59°-86° F (15°-30° C)
- mfd. in the USA for B.F. Ascher & Co., Inc.

INACTIVE INGREDIENT

Inactive ingredients aloe barbadensis (aloe vera gel), SD alcohol 40, and water

Questions?

1-800-324-1880, 7:30am - 4:00pm Central, Mon. - Fri., or visit www.bfascher.com

PACKAGE LABEL

Itch-X Spray PDP